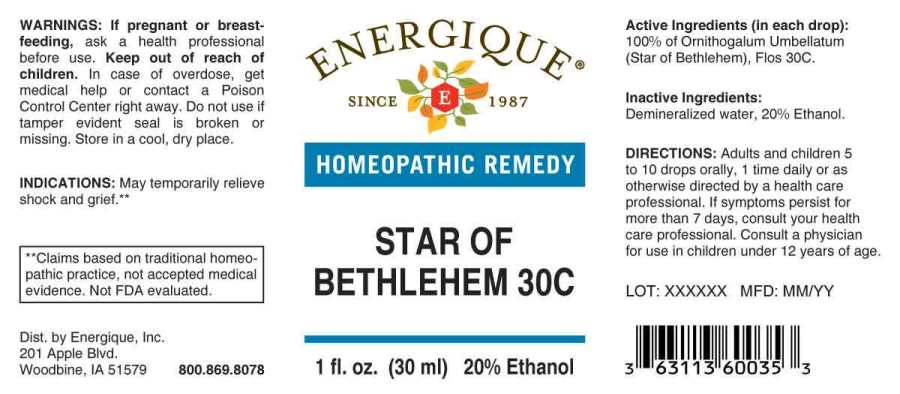 DRUG LABEL: Star of Bethlehem
NDC: 44911-0090 | Form: LIQUID
Manufacturer: Energique, Inc.
Category: homeopathic | Type: HUMAN OTC DRUG LABEL
Date: 20241030

ACTIVE INGREDIENTS: ORNITHOGALUM UMBELLATUM WHOLE 30 [hp_C]/1 mL
INACTIVE INGREDIENTS: WATER; ALCOHOL

DRUG FACTS:

ACTIVE INGREDIENTS:

(in each drop): 100% of Ornithogalum Umbellatum (Star of Bethlehem), Flos 30C.

INDICATIONS:

May temporarily relieve shock and grief.**

**Claims based on traditional homeopathic practice, not accepted medical evidence. Not FDA evaluated.

WARNINGS:

If pregnant or breast-feeding, ask a health professional before use.

Keep out of reach of children. In case of overdose, get medical help or contact a Poison Control Center right away.

Do not use if tamper evident seal is broken or missing.

Store in a cool, dry place.

DIRECTIONS:

Adults and children 5 to 10 drops orally, 1 time daily or as otherwise directed by a health care professional. If symptoms persist for more than 7 days, consult your health care professional. Consult a physician for use in children under 12 years of age.

INACTIVE INGREDIENTS:

Demineralized water, 20% Ethanol

Keep out of reach of children. In case of overdose, get medical help or contact a Poison Control Center right away.

INDICATIONS:

May temporarily relieve shock and grief.**

**Claims based on traditional homeopathic practice, not accepted medical evidence. Not FDA evaluated.

QUESTIONS:

Dist. by Energique, Inc.

201 Apple Blvd.

Woodbine, IA 51579 800.869.8078

PACKAGE DISPLAY LABEL:

ENERGIQUE

SINCE 1987

HOMEOPATHIC REMEDY

STAR OF BETHLEHEM 30C

1 fl. oz. (30 mL) 20% Ethanol